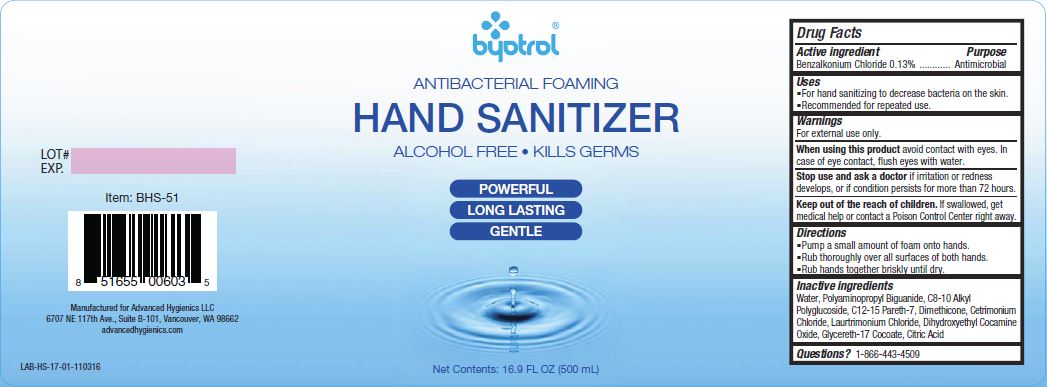 DRUG LABEL: Byotrol Hand Sanitizer
                
NDC: 63002-002 | Form: LIQUID
Manufacturer: Advanced Hygienics LLC
Category: otc | Type: HUMAN OTC DRUG LABEL
Date: 20171214

ACTIVE INGREDIENTS: BENZALKONIUM CHLORIDE 1.3 mg/1 mL
INACTIVE INGREDIENTS: WATER; CETRIMONIUM CHLORIDE; LAURTRIMONIUM CHLORIDE; GLYCERETH-17 COCOATE; DIHYDROXYETHYL COCAMINE OXIDE; POLIHEXANIDE; CAPRYLYL GLUCOSIDE; C12-15 PARETH-7; CITRIC ACID MONOHYDRATE; DIMETHICONE

Drug Facts

Active ingredient

Benzalkonium Chloride 0.13%

Purpose

Antimicrobial

Uses

For hand sanitizing to decrease bacteria on the skin.

Recommended for repeated use.

Warnings

For external use only.

When using this product avoid contact with eyes.

In case of eye contact, flush eyes with water.

Stop use and ask a doctor if irritation or redness develops, or if condition persists for more than 72 hours.

Keep out of reach of children.

If swallowed, get medical help or contact a Poison Control Center right away.

Directions

Pump a small amount of foam onto hands.

Rub thoroughly over all surfaces of both hands.

Rub hands together briskly until dry.

Inactive ingredients:

Water, Polyaminopropyl Biguanide, C8-10 Alkyl Polyglucoside, C12-15 Pareth-7, Dimethicone, Cetrimonium Chloride, Laurtrimonium Chloride, Dihydroxyethyl Cocamine Oxide, Glycereth-17 Cocoate, Citric Acid.

Questions? 1-866-443-4509

PACKAGE LABEL

byotrol

ANTIBACTERIAL FOAMING

HAND SANITIZER

ALCOHOL FREE KILLS GERMS

POWERFUL

LONG LASTING

GENTLE

Net Contents: 16.9 FL OZ (500mL)